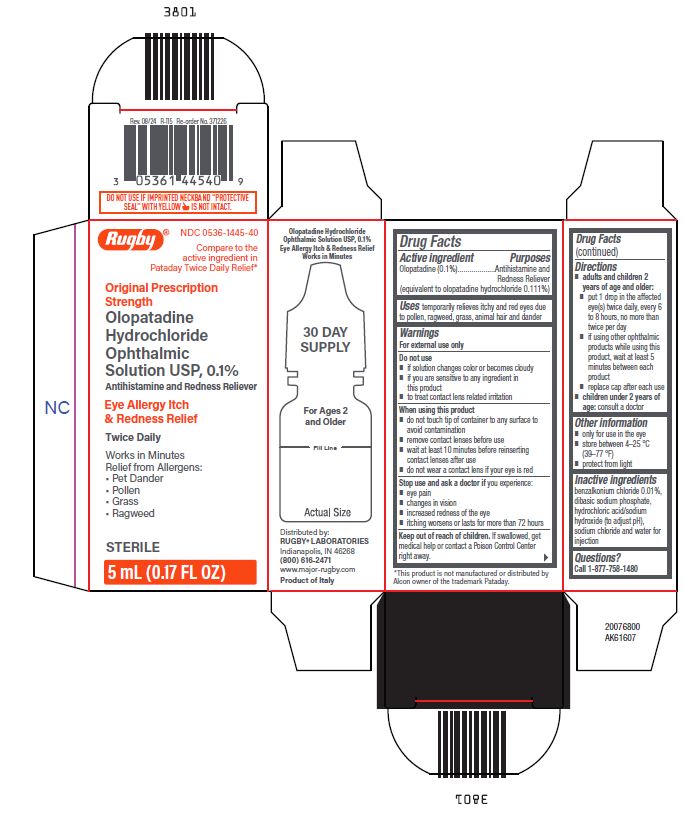 DRUG LABEL: Rugby Olopatadine Hydrochloride Ophthalmic Solution
NDC: 0536-1445 | Form: SOLUTION
Manufacturer: RUGBY LABORATORIES
Category: otc | Type: HUMAN OTC DRUG LABEL
Date: 20260216

ACTIVE INGREDIENTS: OLOPATADINE HYDROCHLORIDE 1 mg/1 mL
INACTIVE INGREDIENTS: BENZALKONIUM CHLORIDE; WATER; SODIUM HYDROXIDE; SODIUM CHLORIDE; HYDROCHLORIC ACID; SODIUM PHOSPHATE, MONOBASIC, UNSPECIFIED FORM

Olopatadine Hydrochloride Ophthalmic Solution USP, 0.1%

Active ingredient

Olopatadine (0.1%)

(equivalent to olopatadine hydrochloride 0.111%)

Purpose

Antihistamine and Redness Reliever

Uses

temporarily relieves itchy and red eyes due to pollen, ragweed, grass, animal hair and dander

Warnings

For external use only

Do not use

- if solution changes color or becomes cloudy
- if you are sensitive to any ingredient in this product
- to treat contact lens related irritation
- When using this product
- do not touch tip of container to any surface to avoid contamination
- remove contact lenses before use
- wait at least 10 minutes before reinserting contact lenses after use
- do not wear a contact lens if your eye is red
- Stop use and ask a doctor ifyou experience:
- eye pain
- changes in vision
- increased redness of the eye
- itching worsens or lasts for more than 72 hours

Keep Out of Reach of Children.

If swallowed, get medical help or contact a Poison Control Center right away.

Directions

- adults and children 2 years of age and older:
- put 1 drop in the affected eye(s) twice daily, every 6 to 8 hours, no more than twice per day
- if using other ophthalmic products while using this product, wait at least 5 minutes between each product
- replace cap after each use
- children under 2 years of age:consult a doctor

Other Information

- only for use in the eye
- store between 4-25 °C (39-77 °F)
- protect from light

Inactive ingredients

benzalkonium chloride 0.01%, dibasic sodium phosphate, hydrochloric acid/sodium hydroxide (to adjust pH), sodium chloride and water for injection

Questions?

Call1-877-758-1480

Package/Label Principal Display Panel

Rugby®

NDC 0536-3445-40

Compare to the

Active ingredient in

Pataday Twice Daily Relief*

Original Prescription

Strength

Olopatadine

Hydrochloride

Ophthalmic

Solution USP, 0.1%

Antihistamine and Redness Reliever

Eye Allergy Itch

& Redness Relief

Twice Daily

Works in Minutes

Relief from Allergens

- Pet Dander
- Pollen
- Grass
- Ragweed

STERILE

5 mL (0.17 FL OZ)

20076800

AK61607